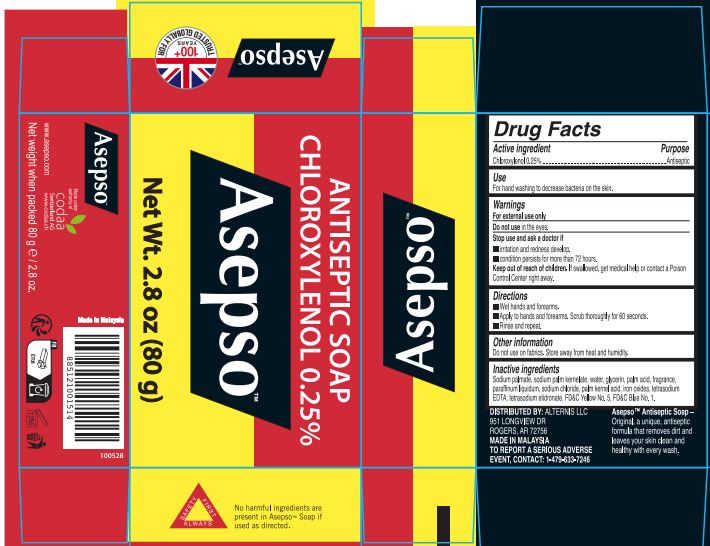 DRUG LABEL: ASEPSO ANTISEPTIC ORIGINAL
NDC: 49698-001 | Form: SOAP
Manufacturer: CODAA Switzerland AG
Category: otc | Type: HUMAN OTC DRUG LABEL
Date: 20231127

ACTIVE INGREDIENTS: CHLOROXYLENOL 2.5 mg/1 g
INACTIVE INGREDIENTS: SODIUM PALMATE; SODIUM PALM KERNELATE; WATER; GLYCERIN; PALM ACID; MINERAL OIL; SODIUM CHLORIDE; PALM KERNEL ACID; FERRIC OXIDE RED; EDETATE SODIUM; ETIDRONATE TETRASODIUM; FD&C YELLOW NO. 5; FD&C BLUE NO. 1

ASEPSO ANTISEPTIC SOAP ORIGINAL

Active ingredient

Chloroxylenol 0.25%

Purpose

Antiseptic

Use

For hand washing to decrease bacteria on the skin.

Warnings

For external use only

Do not use

in the eyes.

Stop use and ask a doctor if

- irritation and redness develop.
- condition persists for more than 72 hours.

Keep out of reach of children.

If swallowed, get medical help or contact a Poison Control Center right away.

Directions

- Wet hands and forearms.
- Apply to hands and forearms. Scrub thoroughly for 60 seconds.
- Rinse and repeat.

Other information

Do not use on fabrics. Store away from heat and humidity.

Inactive ingredients

Sodium palmate, sodium palm kernelate, water, glycerin, palm acid, fragrance, paraffinum liquidum, sodium chloride, palm kernel acid, iron oxides, tetrasodium EDTA, tetrasodium etidronate, FD&C Yellow No. 5, FD&C Blue No. 1.